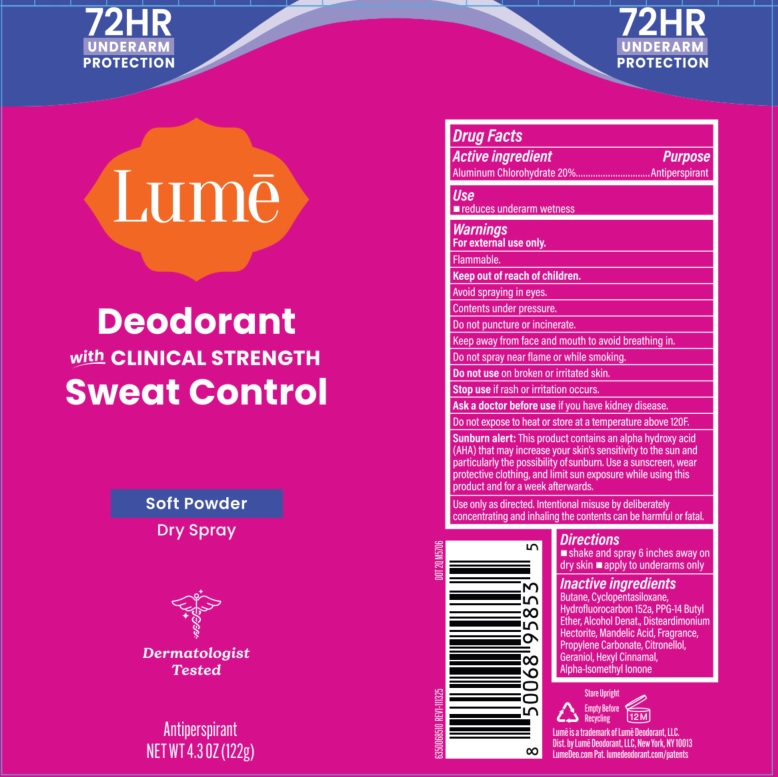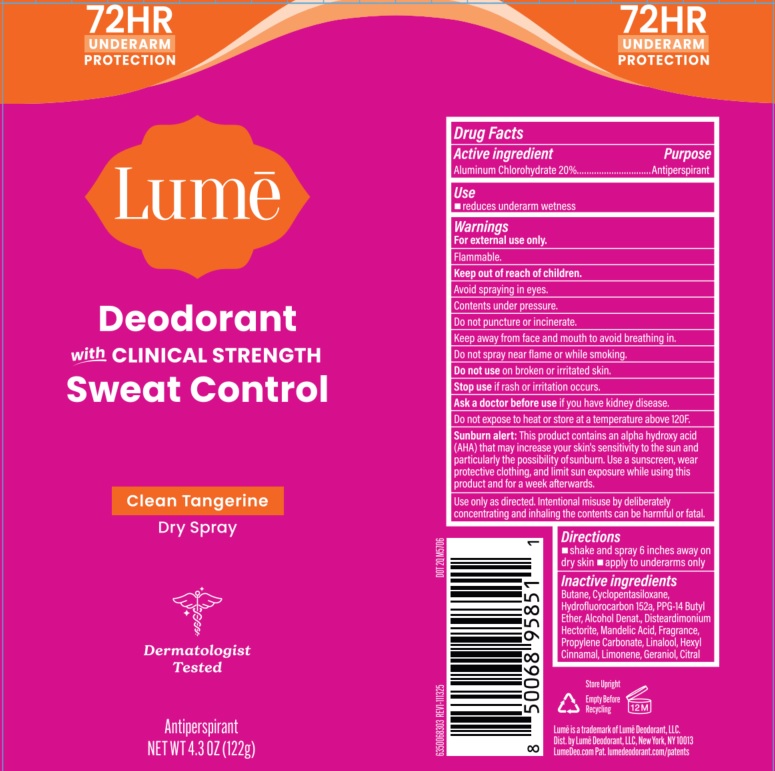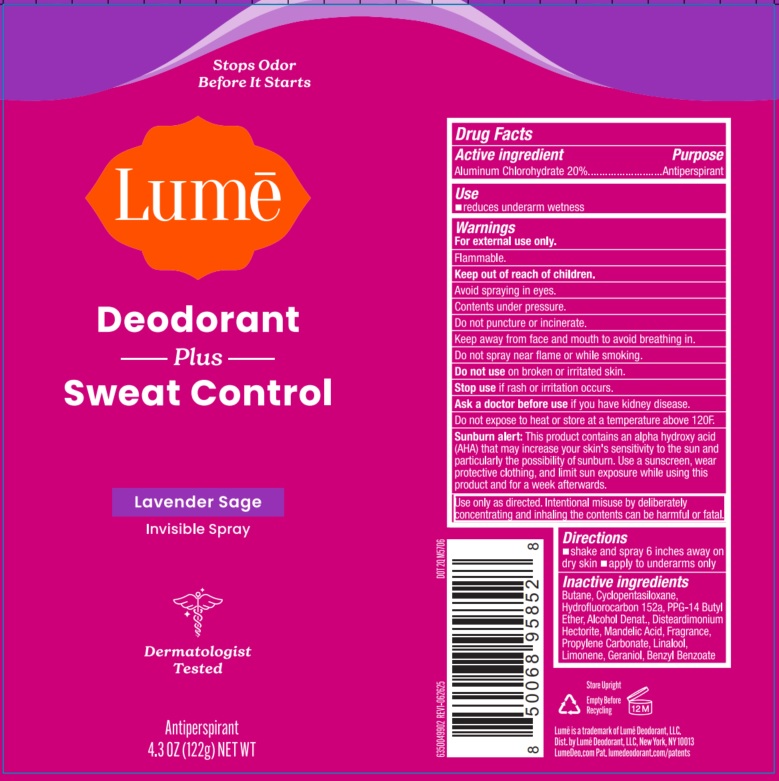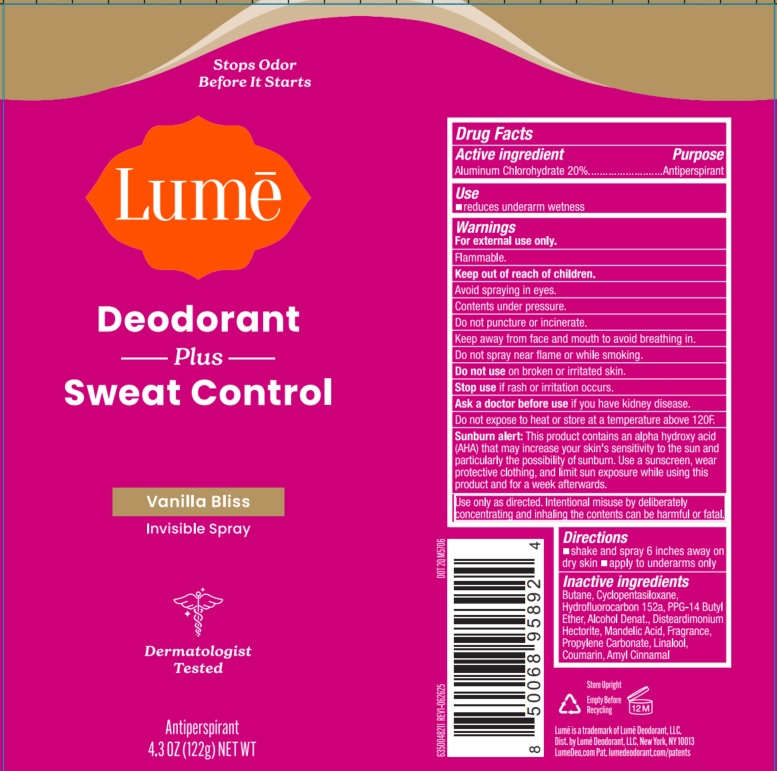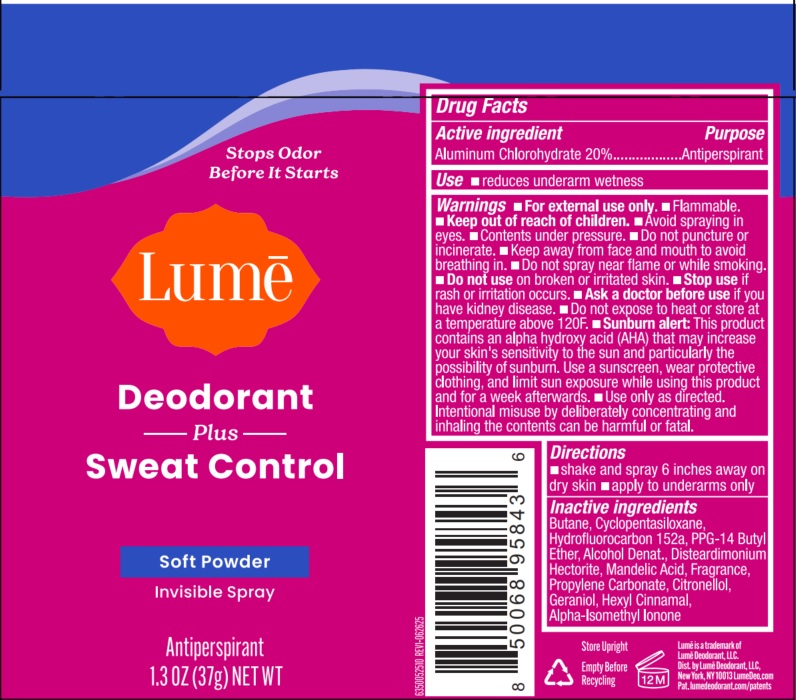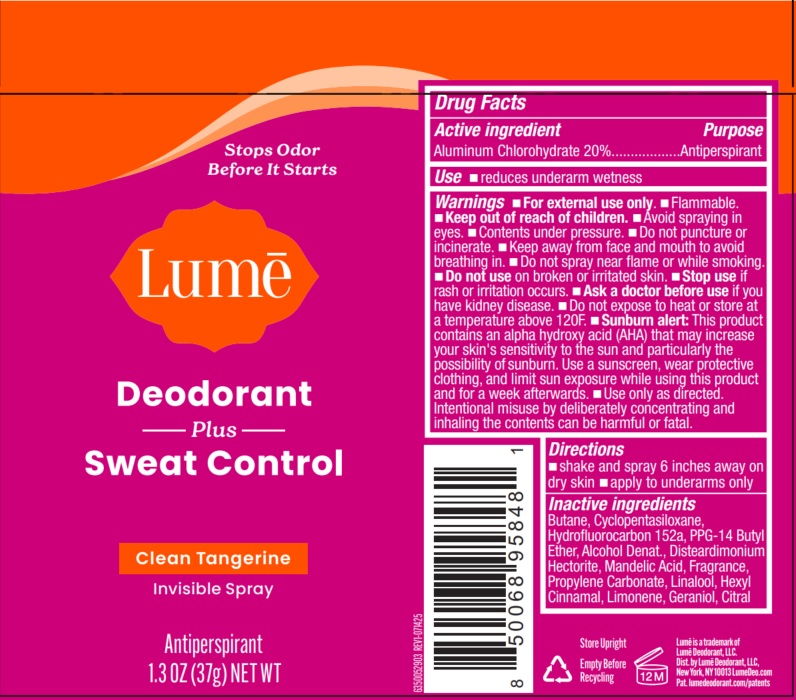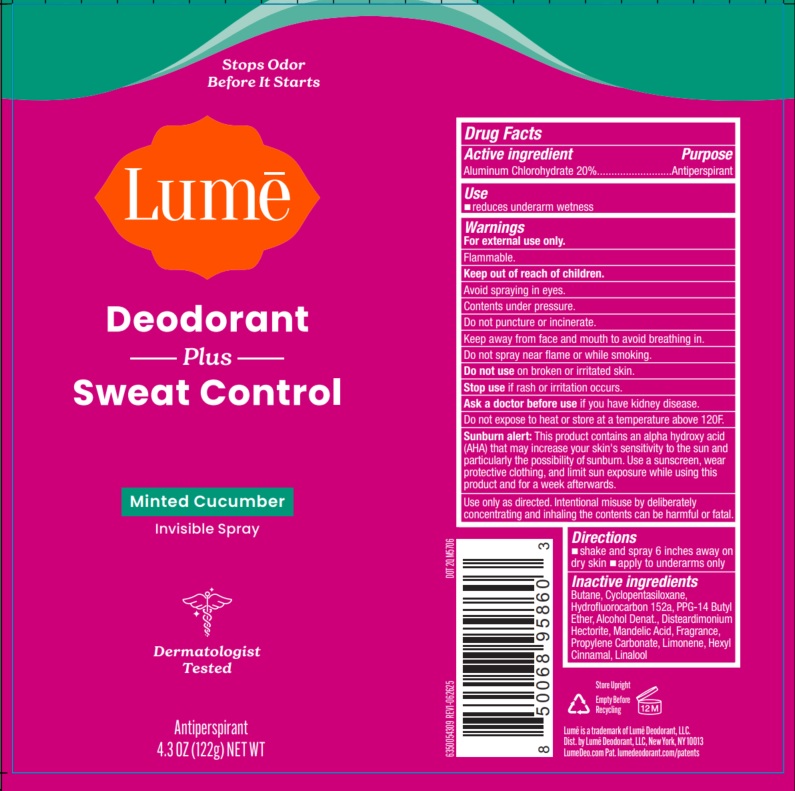 DRUG LABEL: Lume

NDC: 84520-013 | Form: AEROSOL, SPRAY
Manufacturer: Lume Deodorant, LLC.
Category: otc | Type: HUMAN OTC DRUG LABEL
Date: 20260209

ACTIVE INGREDIENTS: ALUMINUM CHLOROHYDRATE 20 g/100 g
INACTIVE INGREDIENTS: GERANIOL; CITRONELLAL; BUTANE; CYCLOPENTASILOXANE; HYDROFLUOROCARBON 152A; PPG-14 BUTYL ETHER; DISTEARDIMONIUM HECTORITE; MANDELIC ACID; PROPYLENE CARBONATE; HEXYL CINNAMAL; ALPHA-ISOMETHYL IONONE; ALCOHOL

Lume

Active ingredient

Aluminum Chlorohydrate 20%

Purpose

Antiperspirant

Use

- reduces underarm wetness

Warnings

For external use only.

Flammable.

Avoid spraying in eyes.

Contents under pressure.

Do not puncture or incinerate.

Keep away fro face and mouth to avoid breathing in.

Do not spray near flame or while smoking.

Do not useon broken or irritated skin.

Stop useif rash or irritation occurs

Ask a doctor before useif you have kidney disease.

Sunburn alert:This product contains an alpha hydroxy acid (AHA) that may increase your skin's sensitivity to the sun and particularly the possibility of sunburn. Use a sunscreen, wear protective clothing, and limit sun expposure while using this product and for a week afterwards.

Do not expose to heat or store at a temperature above 120F.

Use only as directed. Intentional misuse by deliberaely concentrating and inhaling the contents can be harmful or fatal.

Keep out of reach of children.

Directions

- shake and spray 6 inches away on dry skin • apply to underarms only

Soft Powder Dry Spray

Inactive ingredientsButane, Cyclopentasiloxane, Hydrofluorocarbon 152a, PPG-14 Butyl Ether, Alcohol Denat., Disteardimonium Hectorite, Mandelic Acid, Fragrance, Propylene Carbonate, Citronellol, Geraniol, Hexyl Cinnamal, Alpha-Isomethyl Ionone

Clean Tangerine Dry Spray

Inactive ingredientsButane, Cyclopentasiloxane, Hydrofluorocarbon 152a, PPG-14 Butyl Ether, Alcohol Denat., Disteardimonium Hectorite, Mandelic Acid, Fragrance, Propylene Carbonate, Linalool, Hexyl Cinnamal, Limonene, Geraniol, Citral

Lavender Sage Invisible Spray

Inactive ingredientsButane, Cyclopentasiloxane, Hydrofluorocarbon 152a, PPG-14 Butyl Ether, Alcohol Denat., Disteardimonium Hectorite, Mandelic Acid, Fragrance, Propylene Carbonate, Linalool, Limonene, Geraniol, Benzyl Benzoate

Vanilla Bliss Invisible Spray

Inactive ingredientsButane, Cyclopentasiloxane, Hydrofluorocarbon 152a, PPG-14 Butyl Ether, Alcohol Denat., Disteardimonium Hectorite, Mandelic Acid, Fragrance, Propylene Carbonate, Linalool, Coumarin, Amyl Cinnamal

Soft Powder Invisible Spray

Inactive ingredientsButane, Cyclopentasiloxane, Hydrofluorocarbon 152a, PPG-14 Butyl Ether, Alcohol Denat., Disteardimonium Hectorite, Mandelic Acid, Fragrance, Propylene Carbonate, Citronellol, Geraniol, Hexyl Cinnamal, Alpha-Isomethyl Ionone

Clean Tangerine Invisible Spray

Inactive ingredientsButane, Cyclopentasiloxane, Hydrofluorocarbon 152a, PPG-14 Butyl Ether, Alcohol Denat., Disteardimonium Hectorite, Mandelic Acid, Fragrance, Propylene Carbonate, Linalool, Coumarin, Amyl CinnamalHexyl Cinnamal, Limonene, Geraniol, Citral

Minted Cucumber Invisible Spray

Inactive ingredientsButane, Cyclopentasiloxane, Hydrofluorocarbon 152a, PPG-14 Butyl Ether, Alcohol Denat., Disteardimonium Hectorite, Mandelic Acid, Fragrance, Propylene Carbonate, Limonene, Hexyl Cinnamal, Linalool

Dist. by Lume Deodorant, LLC, New York, NY 10013